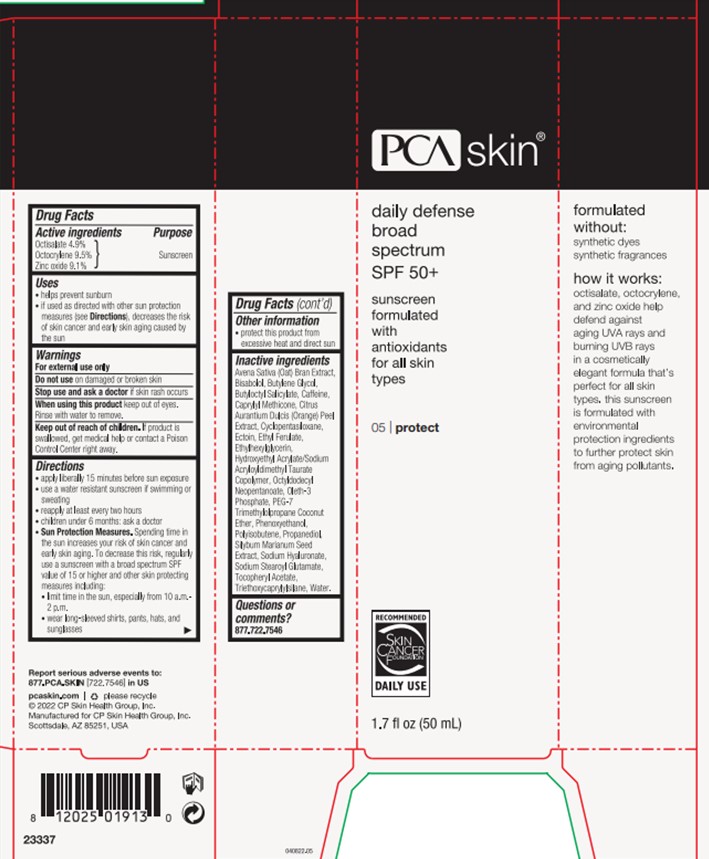 DRUG LABEL: Daily Defense
NDC: 68726-265 | Form: LOTION
Manufacturer: CP Skin Health Group, Inc.
Category: otc | Type: HUMAN OTC DRUG LABEL
Date: 20240214

ACTIVE INGREDIENTS: OCTISALATE 5 g/100 mL; ZINC OXIDE 9.1 g/100 mL; OCTOCRYLENE 10 g/100 mL
INACTIVE INGREDIENTS: CAFFEINE; OLETH-3 PHOSPHATE; BUTYLOCTYL SALICYLATE; PHENOXYETHANOL; ETHYLHEXYLGLYCERIN; ETHYL FERULATE; CAPRYLYL TRISILOXANE; .ALPHA.-TOCOPHEROL ACETATE; CYCLOMETHICONE 5; OCTYLDODECYL NEOPENTANOATE; WATER; ORANGE PEEL; HYALURONATE SODIUM; PROPANEDIOL; ECTOINE; HYDROXYETHYL ACRYLATE/SODIUM ACRYLOYLDIMETHYL TAURATE COPOLYMER (100000 MPA.S AT 1.5%); POLYISOBUTYLENE (1000 MW); SODIUM STEAROYL GLUTAMATE; LEVOMENOL; BUTYLENE GLYCOL; MILK THISTLE; OAT BRAN; TRIETHOXYCAPRYLYLSILANE

PCA Skincare Daily Defense SPF 50

Active Ingredients

Octisalate (4.9%)

Octocrylene (9.5%)

Zinc Oxide (9.1%)

Purpose

Sunscreen

Uses

Helps prevent sunburn

If used as directed with other sun protection measures (see Directions), decreases the risk of skin cancer and early skin aging caused by the sun

Warnings

For external use only

Do not use on damaged or broken skin

Stop use and ask a doctor if skin rash occurs

When using this product keep out of eyes. Rinse with water to remove.

Keep out of reach of children. If product is swallowed, get medical help or contact a Poison Control Center right away

Directions

-Apply liberally 15 minutes before sun exposure

- Use a water resistant sunscreen if swimming or sweating

-Reapply at least every two hours

-Children under 6 months: ask a doctor

-Sun Protectin Measures. Spending time in the sun increases your risk of skin cancer and early skin aging. To decrease this risk, regularly use a sunscreen with a broad spectrum SPF value of 15 or higher and other skin protecting measures including:

- limit time in the sun, especially from 10 a.m. - 2 p.m.
- wear long-sleeved shirts, pants, hats, and sunglasses

Other informaiton

Protect this product from excessive heat and direct sun

Inactive ingredients

Avena Sativa (Oat) Bran Extract

Bisabolol

Butylene Glycol

Butyloctyl Salicylate

Caffeine

Caprylyl Methicone

Citrus Aurantium Dulcis (Orange) Peel Extract

Cyclopentasiloxane

Ectoin

Ethyl Ferulate

Ethylhexylglycerin

Hydroxyethyl Acrylate/Sodium Acryloyldimethyl Taurate Copolymer

Octyldodecyl Neopentanoate

Oleth-3 Phosphate

PEG-7 Trimethylolpropane Coconut Ether

Phenoxyethanol

Polyisobutene

Propanediol

Silybum Marianum Seed Extract

Sodium Hyaluronate

Sodium Stearoyl Glutamate

Tocopheryl Acetate

Triethoxycaprylylsilane

Water

Questions or Comments?

877.722.7546